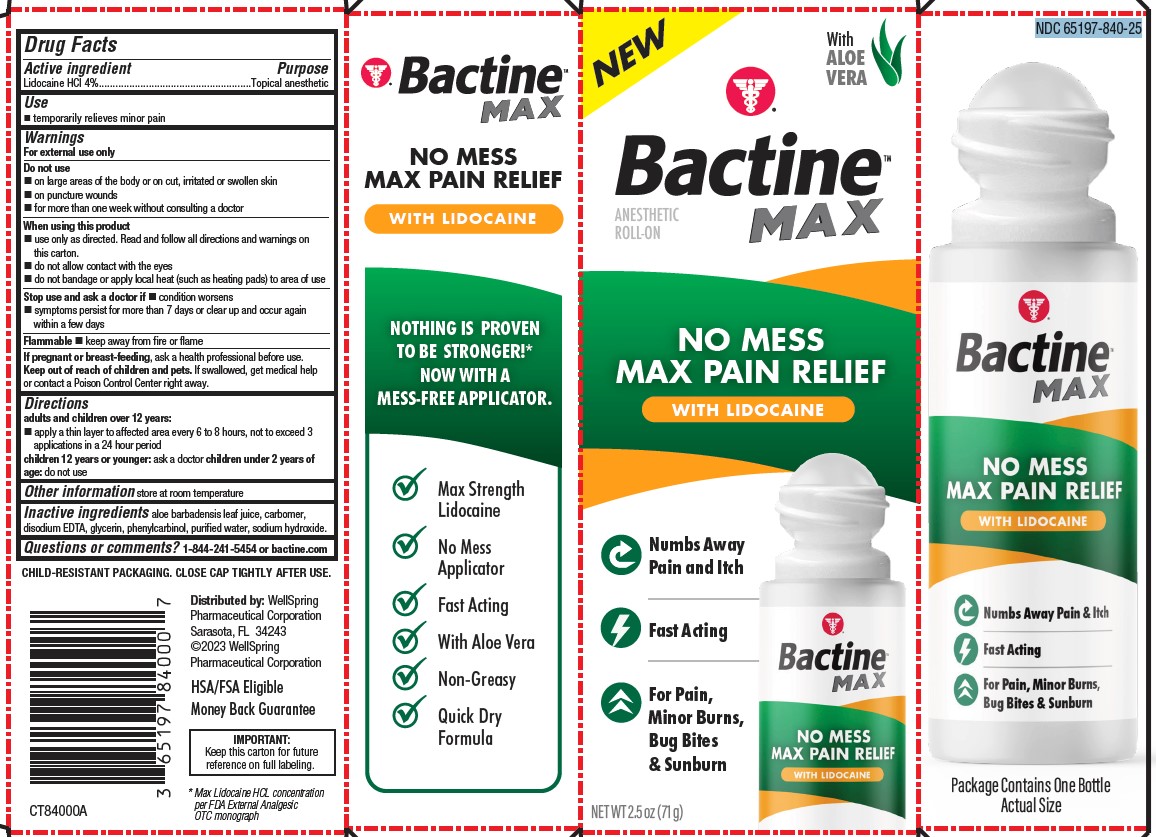 DRUG LABEL: Bactine Max Lidocaine Roll-on 2.5oz
NDC: 65197-840 | Form: LIQUID
Manufacturer: WellSpring Pharmaceutical Corporation
Category: otc | Type: HUMAN OTC DRUG LABEL
Date: 20230425

ACTIVE INGREDIENTS: LIDOCAINE HYDROCHLORIDE 4 g/100 g
INACTIVE INGREDIENTS: WATER; EDETATE DISODIUM; GLYCERIN; SODIUM HYDROXIDE; ALOE VERA LEAF; BENZYL ALCOHOL; CARBOMER HOMOPOLYMER TYPE B (ALLYL PENTAERYTHRITOL CROSSLINKED)

Bactine® Max NO MESS MAX PAIN RELIEF WITH LIDOCAINE

Active Ingredients (w/w)

Lidocaine HCl 4%

Purpose

Topical anesthetic

Uses

temporarily relieves minor pain

Warnings

For external use only

Do not use

- on large areas of the body or on cut, irritated or swollen skin
- on puncture wounds
- for more than one week without consulting a doctor

When using this product

- use only as directed. Read and follow all directions and warnings on this carton.
- do not allow contact with the eyes
- do not bandage or apply local heat (such as heating pads) to area of use

Stop use and ask a doctor if

- condition worsens
- symptoms persist for more than 7 days, or clear up and occur again within a few days

Flammable

- keep away from fire or flame

If pregnant or breast-feeding

ask a health professional before use.

Keep out of reach of children and pets

- If swallowed, get medical help or contact a Poison Control Center right away.

Directions

- adults and children 2 years of age and older:
- apply a thin layer to affected area every 6 to 8 hours, not to exceed 3 applications in a 24 hour period
- children 12 years or younger: ask a doctor
- children under 2 years of age: do not use

Other information

Store at room temperature

Inactive ingredients

aloe barbadensis leaf juice, carbomer, disodium EDTA, glycerin, phenylcarbinol, purified water, sodium hydroxide.

Questions?

1-844-241-5454 or Bactine.com

Distributed by:

WellSpring Pharmaceutical Corporation

Sarasota, FL 34243

© 2023 WellSpring Pharmaceutical Corporation

PACKAGE LABEL. PRINCIPAL DISPLAY PANEL

NO MESS MAX PAIN RELIEF WITH LIDOCAINE

Numbs Away Pain and Itch

Fast Acting

For Pain, Minor Burns, Bug Bites & Sunburn

Max Strength Lidocaine

No Mess Applicator

Fast Acting

With Aloe Vera

Non-Greasy

Quick Dry Formula

HSA/FSA Eligible

MONEY BACK GUARANTEE

IMPORTANT:
Keep this carton for future reference on full labeling.

* Max Lidocaine HCL concentration per FDA External Analgesic OTC monograph

NDC 65197-840-25
Bactine Max Roll-on Artwork

Back Panel

New

Bactine Max

Liquid Bandage with Lidocaine

SHAKE WELL

Bactine Max Liquid Bandageʼs unique formula provides maximum strength pain relief with LIDOCAINE, kills 99.9% of germs*, and protects hard-to-cover minor cuts and scrapes. This flexible bandage dries clear quickly and is breathable to maximize healing.